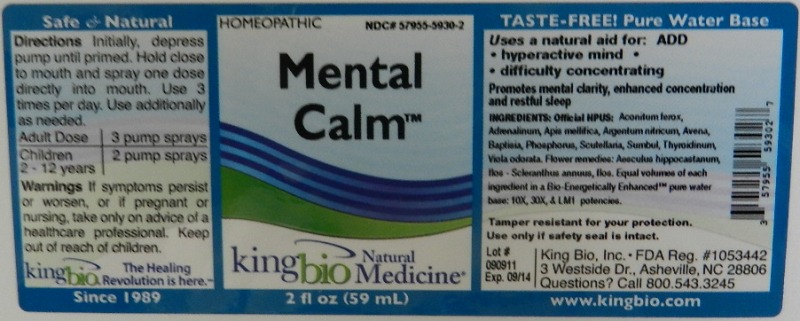 DRUG LABEL: Mental Calm
NDC: 57955-5930 | Form: LIQUID
Manufacturer: King Bio Inc.
Category: homeopathic | Type: HUMAN OTC DRUG LABEL
Date: 20111128

ACTIVE INGREDIENTS: ACONITUM FEROX ROOT 10 [hp_X]/59 mL; EPINEPHRINE 10 [hp_X]/59 mL; APIS MELLIFERA 10 [hp_X]/59 mL; SILVER NITRATE 10 [hp_X]/59 mL; AVENA SATIVA FLOWERING TOP 10 [hp_X]/59 mL; BAPTISIA TINCTORIA ROOT 10 [hp_X]/59 mL; PHOSPHORUS 10 [hp_X]/59 mL; SCUTELLARIA LATERIFLORA 10 [hp_X]/59 mL; FERULA SUMBUL ROOT 10 [hp_X]/59 mL; THYROID, UNSPECIFIED 10 [hp_X]/59 mL; VIOLA ODORATA 10 [hp_X]/59 mL; AESCULUS HIPPOCASTANUM FLOWER 10 [hp_X]/59 mL; SCLERANTHUS ANNUUS FLOWERING TOP 10 [hp_X]/59 mL
INACTIVE INGREDIENTS: WATER

Mental Calm

Active Ingredients

Aconitum Ferox, Adrenalinum, Apis Mellifica, Argentum Nitricum, Avena Sativa, Baptisia Tinctoria, Phosphorus, Scutellaria Lateriflora, Sumbul, Thyroidinum, Viola Odorata, Aesculus Hippocastanum, Flos and Scleranthus Annuus, Flos.

Reference image mental calm.jpg

Inactive Ingredient

Equal volumes of each ingredient in a Bio-Energetically Enhanced pure water base: 10X, 30X and LM1 potencies.

Reference image mental calm.jpg

Purpose

Uses an natural aid for ADD: hyperactive mind, forgetfulness, difficulty concentrating.

Promotes mental clarity, enhanced concentration and restful sleep.

Reference image mental calm.jpg

Dosage and Administration

Direction Initially, depress pump until primed. Hold close to mouth and spray one dose directly into mouth. Use 3 times per day. Use additionally as needed.

Adult Dose 3 pump sprays

Children (2-12 years) 2 pump sprays

Reference image mental calm.jpg

Warnings

If symptoms persist or worsen, or if pregnant or nursing, take only on advice of a healthcare professional. Keep out of reach of children.

Other: Tamper resistant for your protection. Use only if safety seal is intact.

Reference image mental calm.jpg

Indications and Usage

Uses an natural aid for:

- ADD
- hyperactive mind
- forgetfulness
- difficulty concentrating

Promotes mental clarity, enhanced concentration and restful sleep.
Reference image mental calm.jpg

Keep out of reach of children.

Reference image mental calm.jpg

PACKAGE LABEL

King Bio Inc.

3 Westside Drive

Asheville, NC 28806

Ouestions? Call 800.543.3245